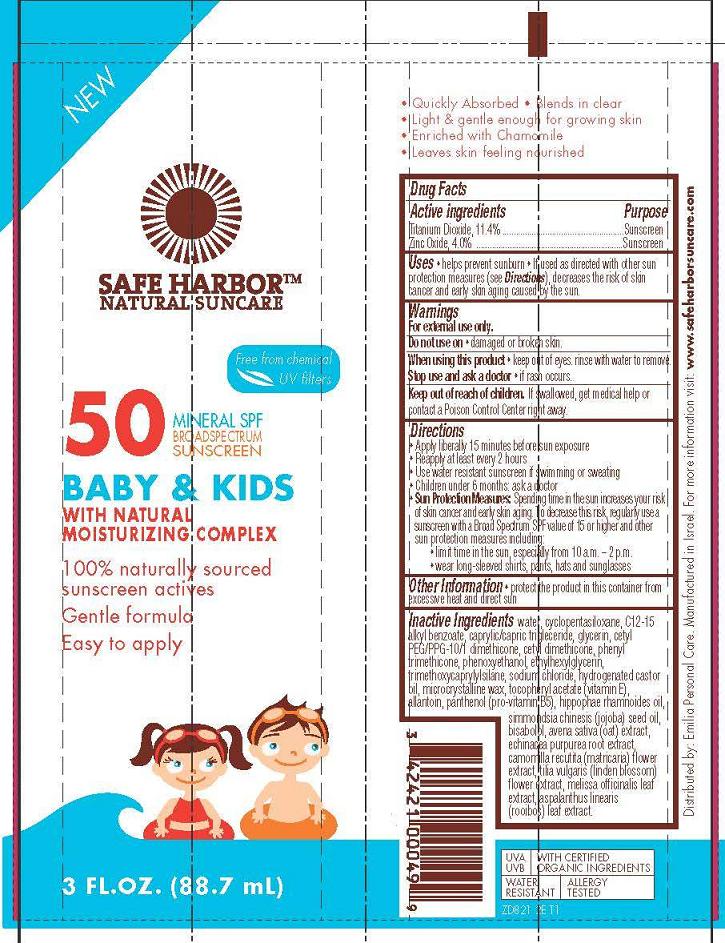 DRUG LABEL: Safe Harbor - Natural Sunscreen - Baby and Kids SPF50 Broad Spectrum Sunscreen
NDC: 42421-821 | Form: CREAM
Manufacturer: Emilia Personal Care Inc.
Category: otc | Type: HUMAN OTC DRUG LABEL
Date: 20131119

ACTIVE INGREDIENTS: TITANIUM DIOXIDE 11.4 g/100 mL; ZINC OXIDE 4 g/100 mL
INACTIVE INGREDIENTS: WATER; CYCLOMETHICONE 5; ALKYL (C12-15) BENZOATE; TRICAPRYLIN; GLYCERIN; CETYL PEG/PPG-10/1 DIMETHICONE (HLB 2); CETYL DIMETHICONE 150; PHENYL TRIMETHICONE; PHENOXYETHANOL; ETHYLHEXYLGLYCERIN; TRIMETHOXYCAPRYLYLSILANE; SODIUM CHLORIDE; HYDROGENATED CASTOR OIL; MICROCRYSTALLINE WAX; .ALPHA.-TOCOPHEROL ACETATE; ALLANTOIN; PANTHENOL; HIPPOPHAE RHAMNOIDES FRUIT OIL; JOJOBA OIL; LEVOMENOL; OAT KERNEL OIL; ECHINACEA PURPUREA ROOT; MATRICARIA CHAMOMILLA FLOWERING TOP OIL; TILIA X EUROPAEA FLOWER; MELISSA OFFICINALIS LEAF; ASPALATHUS LINEARIS LEAF

Safe Harbor Natural Suncare

Active ingredient

Titanium Dioxide 11.4%
Zinc Oxide 4.0%

Purpose

Sunscreen

Uses

- helps prevent sunburn
- If used as directed with other sun protections measures (see Directions), decreases the risk of skin cancer and early skin aging caused by the sun.

Warnings

For external use only.

Do not use on

- damaged or broken skin

When using this product

- keep out of eyes. rinse with water to remove

Stop use and ask a doctor

- if rash occurs

Keep Out of Reach of Children

If swallowed, get medical help or contact a Poison Control Center right away.

Directions

- Apply liberally 15 minutes before sun exposure
- Reapply at least every 2 hours
- Use water resistant sunscreen if swimming or sweating
- Children under 6 months: ask a doctor
- Sun Protection Measures: Spending time in the sun increases your risk of sun cancer and early skin aging. To decrease this risk, regularly use a sunscreen with a Broad Spectrum SPF value of 15 or higher and other sun protection measures including:
  - limit time in the sun, especially from 10a.m. - 2p.m.
  - wear long-sleeved shirts, pants, hats, and sunglasses

Other information

- protect the product in this container from excessive heat and direct sun

Inactive ingredients

water, cyclopentasiloxane, C12-15 alkyl benzoate, caprylic/capric triglyceride, glycerin, cetyl PEG/PPG-10/1 dimethicone, cetyl dimethicone, phenyl trimethicone, phenoxyethanol, ethylhexylglycerin, trimethoxycaprylylsilane, sodium chloride, hydrogenated castor oil, microcrystaline wax, tocopheryl acetate (vitamin E), allantoin, panthenol (pro-vitamin B5), hippophae rhamnoides oil, simmondsia chinesis (jojoba) seed oil, bisabolol, avena sativa (oat) extract, echinacea purpurea root extract, camomilla recutita (matricaria) flower extract, tilia vulgaris (linden blossom) flower extract, melissa officinalis leaf extract, aspalanthus linearis (rooibos) leaf extract

Package/Label Principal Display Panel

Safe Harbor™ Natural Suncare

Free from chemical UV filters

50 Mineral SPF Broad Spectrum Sunscreen

Baby & Kids
With Natural Moisturizing Complex

100% naturally sourced sunscreen actives

Gentle formula

Easy to apply

3 Fl. Oz (88.7 mL)

Distributed by: Emilia Personal Care.
Manufactured in Israel.
For more information visit: www.safeharborsuncare.com

UVA, UVB
With Certified Organic Ingredients
Water Resistant
Allergy Tested

ZD821 2E T1

Label